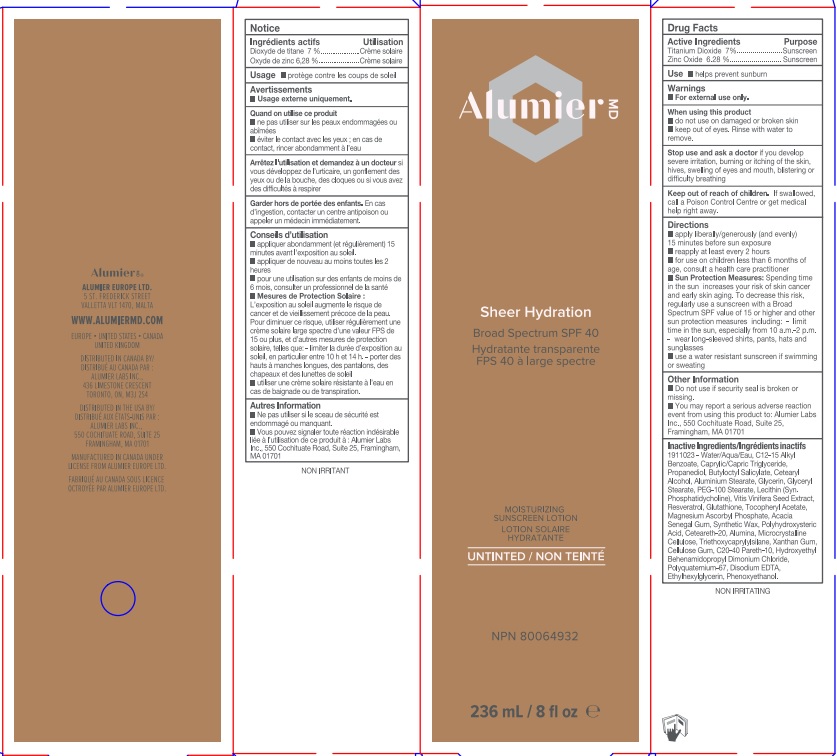 DRUG LABEL: Alumier MD Sheer Hydration
NDC: 69473-006 | Form: LOTION
Manufacturer: Alumier Labs
Category: otc | Type: HUMAN OTC DRUG LABEL
Date: 20241212

ACTIVE INGREDIENTS: ZINC OXIDE 62.8 mg/1 mL; TITANIUM DIOXIDE 70 mg/1 mL
INACTIVE INGREDIENTS: MEDIUM-CHAIN TRIGLYCERIDES; ALUMINUM MONOSTEARATE; TRIETHOXYCAPRYLYLSILANE; WATER; CETOSTEARYL ALCOHOL; GLYCERYL MONOSTEARATE; PEG-100 STEARATE; ACACIA; POLYOXYL 20 CETOSTEARYL ETHER; ALUMINUM OXIDE; XANTHAN GUM; HYDROXYETHYL BEHENAMIDOPROPYL DIMONIUM CHLORIDE; ALKYL (C12-15) BENZOATE; PROPANEDIOL; GLUTATHIONE; MAGNESIUM ASCORBYL PHOSPHATE; MICROCRYSTALLINE CELLULOSE; EDETATE DISODIUM; CARBOXYMETHYLCELLULOSE SODIUM, UNSPECIFIED FORM; C20-40 PARETH-10; ETHYLHEXYLGLYCERIN; PHENOXYETHANOL; BUTYLOCTYL SALICYLATE; GLYCERIN; VITIS VINIFERA SEED; RESVERATROL; .ALPHA.-TOCOPHEROL ACETATE

Alumier MD Sheer Hydration

Active Ingredients

Titanium Dioxide 7%

Zinc Oxide 6.28%

Purpose

Sunscreen

Use

- helps prevent sunburn

Warnings

- For external use only.

When using this product

- do not use on damaged or broken skin
- keep out of eyes. Rinse with water to remove.

Stop use and ask a doctor if you develop severe irritation, burning or itching of the skin, hives, swelling of eyes and mouth, blistering or difficulty breathing

Keep out of reach of children. If swallowed, call a Poison Control Centre or get medical help right away.

Directions

- apply liberally/generously (and evenly) 15 minutes before sun exposure
- reapply at least every 2 hours
- for use on children less than 6 months of age, consult a health care practitioner
- Sun Protection Measures: Spending time in the sun increases your risk of skin cancer and early skin aging. To decrease this risk, regularly use a sunscreen with a Broad Spectrum SPF value of 15 or higher and other sun protection measures including: - limit time in the sun, especially from 10 a.m.-2 p.m. - wear long-sleeved shirts, pants, hats and sunglasses
- use a water resistant sunscreen if swimming or sweating

Other Information

- Do not use if security seal is broken or missing.
- You may report a serious adverse reaction event from using this product to: Alumier Labs Inc., 550 Cochituate Road, Suite 25, Framingham, MA 01701

Inactive Ingredients

Water/Aqua/Eau, C12-15 Alkyl Benzoate, Caprylic/Capric Triglyceride, Propanediol, Butyloctyl Salicylate, Cetearyl Alcohol, Aluminium Stearate, Glycerin, Glyceryl Stearate, PEG-100 Stearate, Lecithin (Syn. Phosphatidycholine), Vitis Vinifera Seed Extract, Resveratrol, Glutathione, Tocopheryl Acetate, Magnesium Ascorbyl Phosphate, Acacia Senegal Gum, Synthetic Wax, Polyhydroxysteric Acid, Ceteareth-20, Alumina, Microcrystalline Cellulose, Triethoxycaprylylsilane, Xanthan Gum, Cellulose Gum, C20-4O Pareth-10, Hydroxyethyl Behenamidopropyl Dimonium Chloride, Polyquatemium-67, Disodium EDTA, Ethylhexylglycerin, Phenoxyethanol.

Product Packaging - 236 mL

Alumier MD

Sheer Hydration

Broad Spectrum SPF 40

MOISTURIZING SUNSCREEN LOTION

UNTINTED

NPN 80064932

236 mL / 8 fl oz